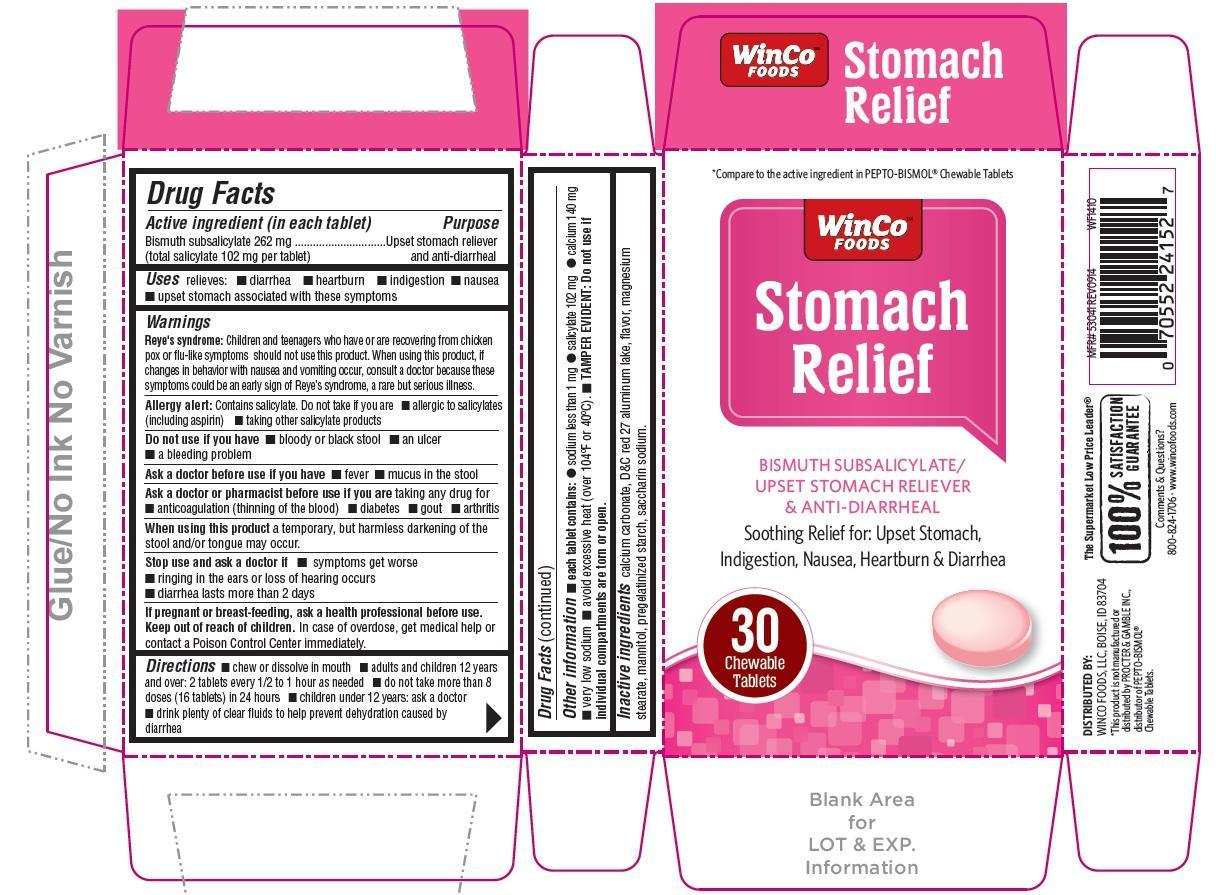 DRUG LABEL: Stomach Relief
NDC: 67091-235 | Form: TABLET, CHEWABLE
Manufacturer: WinCo Foods, LLC
Category: otc | Type: HUMAN OTC DRUG LABEL
Date: 20220114

ACTIVE INGREDIENTS: BISMUTH SUBSALICYLATE 262 mg/1 1
INACTIVE INGREDIENTS: CALCIUM CARBONATE; D&C RED NO. 27; MAGNESIUM STEARATE; MANNITOL; STARCH, CORN; SACCHARIN SODIUM

Stomach Relief Chewable Tablets

Active ingredient (in each tablet)

Bismuth subsalicylate 262 mg

(total salicylate 102 mg per tablet)

Purpose

Upset stomach reliever and anti-diarrheal

Uses

relieves:

- diarrhea
- heartburn
- indigestion
- nausea
- upset stomach associated with these symptoms

Warnings

Reye's syndrome: Children and teenagers who have or are recovering from chicken pox or flu-like symptoms should not use this product. when using this product , if changes in behavior with nausea and vomiting occur, consult a doctor because these symptoms could be an early sign of Reye's syndrome, a rare but serious illness.

Allergy alert: Contains salicylate. Do not take if you are

- allergic to salicylates (including aspirin)
- taking other salicylate products

Do not use if you have

- bloody or black stool
- an ulcer
- a bleeding problem

Ask a doctor before use if you have

- fever
- mucus in the stool

Ask a doctor or pharmacist before use if you are taking any drug for

- anticoagulation (thinning of the blood)
- diabetes
- gout
- arthritis

When using this product

a temporary, but harmless darkening of the stool and/or tongue may occur.

Stop use and ask a doctor if

- symptoms get worse
- ringing in the ears or loss of hearing occurs
- diarrhea lasts more than 2 days

If pregnant or breast-feeding, ask a health professional before use.

Keep out of reach of children. In case of overdose, get medical help or contact a Poison Control Center immediately.

Directions

- chew or dissolve in mouth
- adults and children 12 years and over: 2 tablets every 1/2 to 1 hour as needed
- do not take more than 8 doses (16 tablets) in 24 hours
- children under 12 years: ask a doctor
- drink plenty of clear fluids to help prevent dehydration caused by diarrhea.

Other information: each tablet contains:

- sodium less than 1 mg
- salicylate 102 mg
- calcium 140 mg
- very low sodium
- avoid excessive heat (over 104˚F or 40˚C)
- TAMPER EVIDENT: Do not use if individual compartments are torn or open.

Inactive ingredients

calcium carbonate, D&C red 27 aluminum lake, flavor, magnesium stearate, mannitol, pregelatinized starch, saccharin sodium.

Principal Display Panel

*Compare to the active ingredient in PEPTO-BISMOL® Chewable Tablets
WinCo Foods

Stomach Relief

BISMUTH SUBSALICYLATE / UPSET STOMACH RELIEVER & ANTI-DIARRRHEAL

Soothing Relief for: Upset Stomach, Indigestion, Nausea, Heartburn & Diarrhea

30 chewable tablets